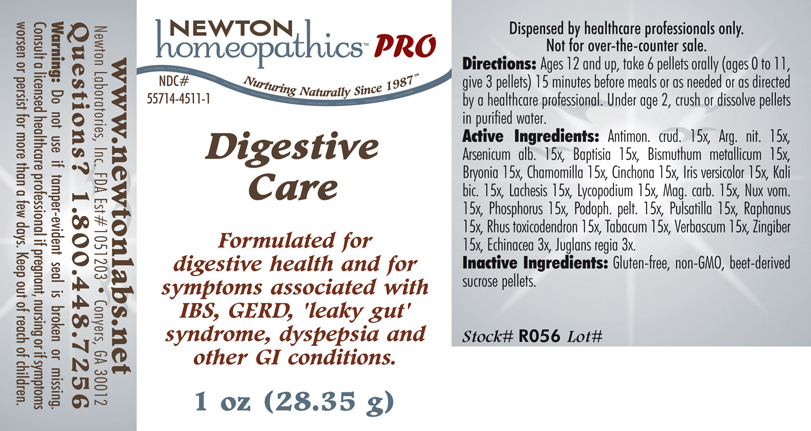 DRUG LABEL: Digestive Care 
NDC: 55714-4511 | Form: PELLET
Manufacturer: Newton Laboratories, Inc.
Category: homeopathic | Type: HUMAN PRESCRIPTION DRUG LABEL
Date: 20110601

ACTIVE INGREDIENTS: Antimony Trisulfide 15 [hp_X]/1 g; Silver Nitrate 15 [hp_X]/1 g; Arsenic Trioxide 15 [hp_X]/1 g; Baptisia Tinctoria Root 15 [hp_X]/1 g; Bismuth 15 [hp_X]/1 g; Bryonia Alba Root 15 [hp_X]/1 g; Matricaria Recutita 15 [hp_X]/1 g; Cinchona Officinalis Bark 15 [hp_X]/1 g; Iris Versicolor Root 15 [hp_X]/1 g; Potassium Dichromate 15 [hp_X]/1 g; Lachesis Muta Venom 15 [hp_X]/1 g; Lycopodium Clavatum Spore 15 [hp_X]/1 g; Magnesium Carbonate 15 [hp_X]/1 g; Strychnos Nux-vomica Seed 15 [hp_X]/1 g; Phosphorus 15 [hp_X]/1 g; Podophyllum 15 [hp_X]/1 g; Pulsatilla Vulgaris 15 [hp_X]/1 g; Daikon 15 [hp_X]/1 g; Toxicodendron Pubescens Leaf 15 [hp_X]/1 g; Tobacco Leaf 15 [hp_X]/1 g; Verbascum Thapsus 15 [hp_X]/1 g; Ginger 15 [hp_X]/1 g; Echinacea, Unspecified 3 [hp_X]/1 g; Juglans Regia Fruit Rind, Immature 3 [hp_X]/1 g
INACTIVE INGREDIENTS: Sucrose

Digestive Care

INDICATIONS & USAGE SECTION

Digestive Care Formulated for digestive health and for symptoms associated with IBS, GERD, 'leaky gut' syndrome, dyspepsia and other GI conditions.

DOSAGE & ADMINISTRATION SECTION

Directions: Ages 12 and up, take 6 pellets orally (ages 0 to 11, give 3 pellets) 15 minutes before meals or as needed or as directed by a healthcare professional. Under age 2, crush or dissolve pellets in purified water.

ACTIVE INGREDIENT SECTION

Antimon. crud. 15x, Arg. nit. 15x, Arsenicum alb. 15x, Baptisia 15x, Bismuthum metallicum 15x, Bryonia 15x, Chamomilla 15x, Cinchona 15x, Iris versicolor 15x, Kali bic. 15x, Lachesis 15x, Lycopodium 15x, Mag. carb. 15x, Nux vom.15x, Phosphorus 15x, Podoph. pelt. 15x, Pulsatilla 15x, Raphanus 15x, Rhus toxicodendron 15x, Tabacum 15x, Verbascum 15x, Zingiber 15x, Echinacea 3x, Juglans regia 3x.

PURPOSE SECTION

Formulated for digestive health and for symptoms associated with IBS, GERD, 'leaky gut' syndrome, dyspepsia and other GI conditions.

INACTIVE INGREDIENT SECTION

Inactive Ingredients: Gluten-free, non-GMO, beet-derived pellets.

QUESTIONS? SECTION

www.newtonlabs.net Newton Laboratories, Inc. FDA Est # 1051203 - Conyers, GA 30012
Questions? 1.800.448.7256

WARNINGS SECTION

Warning: Do not use if tamper - evident seal is broken or missing. Consult a licensed healthcare professional if pregnant, nursing or if symptoms worsen or persist for more than a few days. Keep out of reach of children.

PREGNANCY OR BREAST FEEDING SECTION

Consult a licensed healthcare professional if pregnant, nursing or if symptoms worsen or persist for more than a few days.

KEEP OUT OF REACH OF CHILDREN SECTION

Keep out of reach of children.